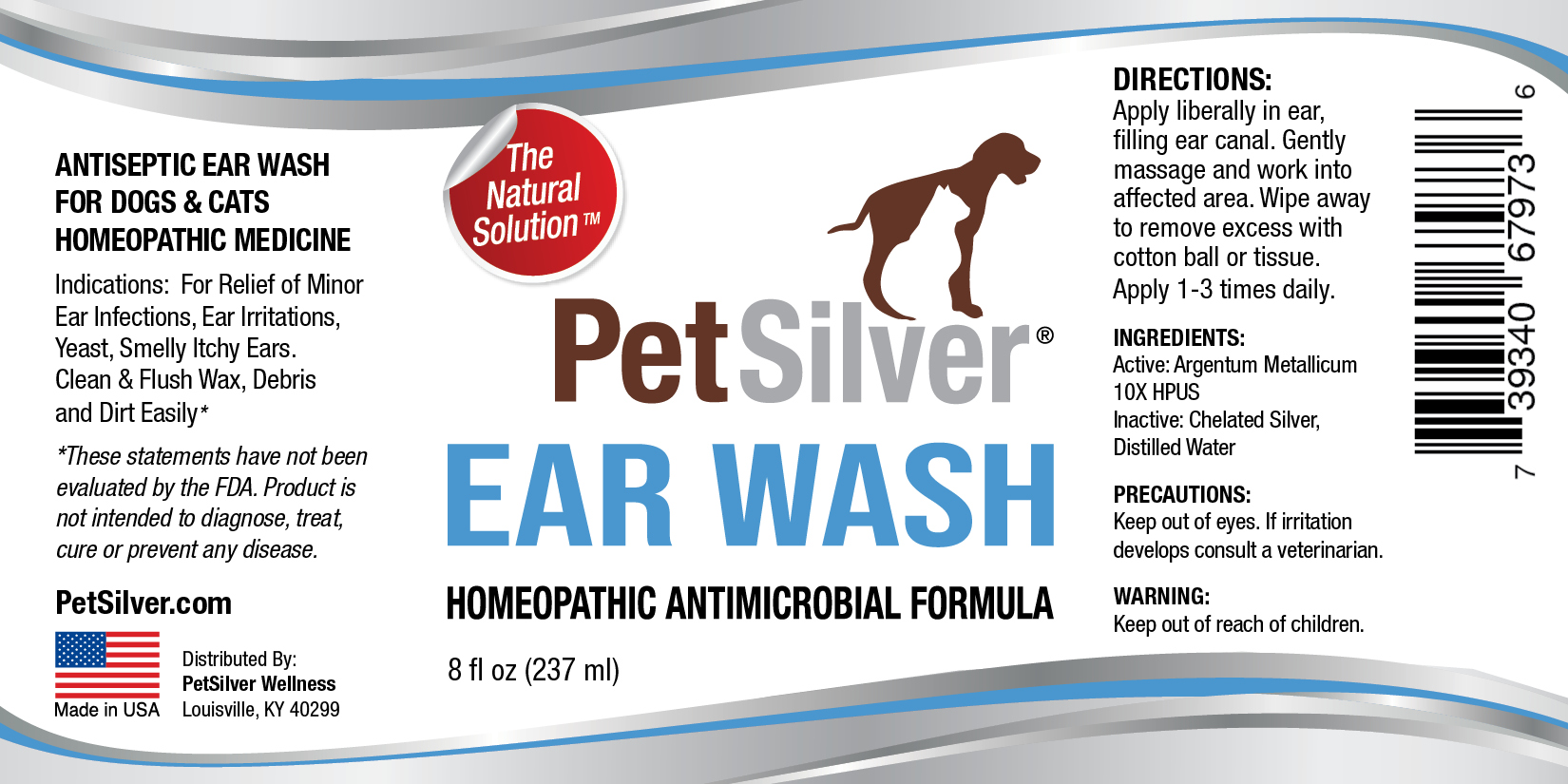 DRUG LABEL: PetSilver Ear Wash 8
NDC: 72363-024 | Form: SPRAY
Manufacturer: AG Essence
Category: homeopathic | Type: HUMAN OTC DRUG LABEL
Date: 20251214

ACTIVE INGREDIENTS: SILVER 0.007 g/237 g
INACTIVE INGREDIENTS: WATER 235.957 g/237 g; ANHYDROUS CITRIC ACID 0.036 g/237 g

PetSilver Ear Wash 8 ounce

DIRECTIONS:

Clean area of dirt and debris. Apply 3-4 sprays to affected area up to 3 times daily. Dress area if needed. Consult your veterinarian if problem persists.

PRECAUTIONS:

Keep out of eyes. If irritation develops consult a veterinarian.

INGREDIENT:

Active: Argentum Metallicum10X HPUS

INGREDIENTS:

Inactive: Chelated Silver, Distilled Water

Indications:

For Relief of Minor Ear infections, Ear irritations, Yeast, Smelly Itchy Ears, Clean & Flush Wax, Debris and Dirt Easily.

WARNING:

Keep out of reach of children.

WARNING:

Keep out of reach of children